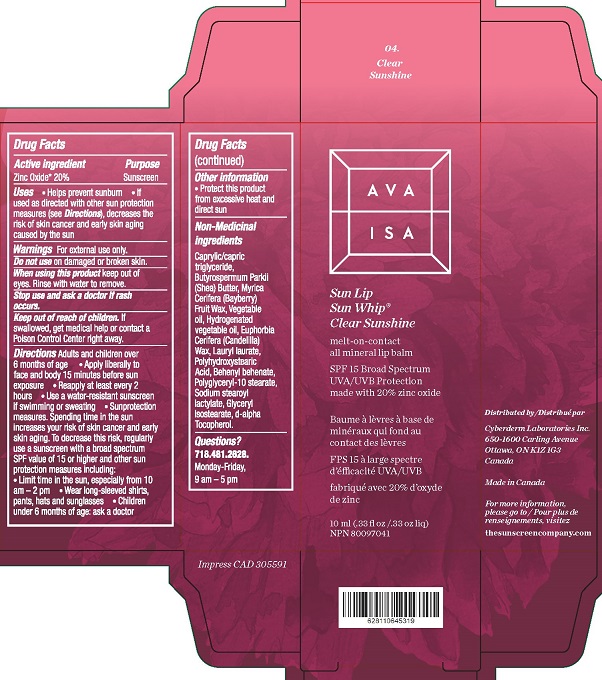 DRUG LABEL: Ava Isa Sun Lip Sun Whip
NDC: 71644-009 | Form: CREAM
Manufacturer: Cyberderm Laboratories inc.
Category: otc | Type: HUMAN OTC DRUG LABEL
Date: 20260101

ACTIVE INGREDIENTS: ZINC OXIDE 20 g/100 mL
INACTIVE INGREDIENTS: .ALPHA.-TOCOPHEROL, D-; MEDIUM-CHAIN TRIGLYCERIDES; GLYCERYL ISOSTEARATE; POLYHYDROXYSTEARIC ACID (2300 MW); SHEA BUTTER; MORELLA CERIFERA FRUIT WAX; SODIUM STEAROYL LACTYLATE; CANDELILLA WAX; LAURYL LAURATE; BEHENYL BEHENATE; POLYGLYCERYL-10 STEARATE; CORN OIL; HYDROGENATED PALM OIL

Ava Isa Sun Whip Lip Balm Clear Sunshine

Drug Facts

Active ingredient

Zinc Oxide* 20%

Purpose

Sunscreen

Uses

- Helps prevent sunburn
- If used as directed with other sun protection measures (see Directions), decreases the risk of skin cancer and early skin aging caused by the sun

Warnings

For external use only.

Do not use on damaged or broken skin.

WHEN USING

When using this productkeep out of eyes. Rinse with water to remove.

Stop use and ask a doctor ifrash occurs.

Keep out of reach of children.If swallowed, get medical help or contact a Poison Control Center right away.

Directions

- Adults and children over 6 months of age
- Apply liberally to face and body 15 minutes before sun exposure
- Reapply at least every 2 hours
- Use a water-resistant sunscreen if swimming or sweating
- Sun Protection Measures. Spending time in the sun increases your risk of skin cancer and early skin aging.To decrease this risk, regularly use a sunscreen with a broad spectrum SPF value of 15 or higher and other sun protection measures including:
- Limit time in the sun, especially from 10am - 2pm
- Wear long-sleeved shirts, pants, hats and sunglasses
- Children under 6 months of age: ask a doctor

Other information

- Protect this product from excessive heat and direct sun

Inactive ingredients

Caprylic/capric triglyceride, Butyrospermum Parkii (Shea) Butter, Myrica Cerifera (Bayberry) Fruit Wax, Vegetable oil, Hydrogenated vegetable oil, Euphorbia Cerifera (Candelilla) Wax, Lauryl laurate, Polyhydroxystearic Acid, Behenyl behenate, Polyglyceryl-10 stearate, Sodium stearoyl lactylate, Glyceryl Isostearate, d-alpha Tocopherol.

Questions?
718-481-2628. Monday-Friday, 9 am - 5 pm

Distributed by

Cyberderm Laboratories, Inc.

650-1600 Carling Avenue

Ottawa, ON K1Z 1G3

Made in Canada

PACKAGE LABEL

AVA ISA
Sun Lip
Sun Whip®
Clear Sunshine
melt-on-contact all mineral lip balm
SPF 15 Broad Spectrum
UVA/UVB Protection
made with 20% zinc oxide
10 ml (.33 fl oz)
NPN 80097041